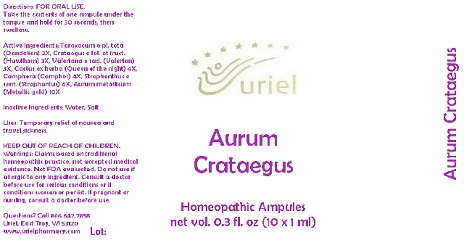 DRUG LABEL: Aurum Crataegus
NDC: 48951-1184 | Form: LIQUID
Manufacturer: Uriel Pharmacy Inc.
Category: homeopathic | Type: HUMAN OTC DRUG LABEL
Date: 20180417

ACTIVE INGREDIENTS: TARAXACUM PALUSTRE ROOT 2 [hp_X]/1 mL; HAWTHORN LEAF WITH FLOWER 3 [hp_X]/1 mL; VALERIAN 3 [hp_X]/1 mL; SELENICEREUS GRANDIFLORUS STEM 4 [hp_X]/1 mL; CAMPHOR (NATURAL) 4 [hp_X]/1 mL; STROPHANTHUS KOMBE WHOLE 6 [hp_X]/1 mL; GOLD 10 [hp_X]/1 mL
INACTIVE INGREDIENTS: WATER; SODIUM CHLORIDE

Aurum Crataegus

INDICATIONS AND USAGE

Directions: FOR ORAL USE.

DOSAGE AND ADMINISTRATION

Take the contents of one ampule under the tongue and hold for 30 seconds, then swallow.

ACTIVE INGREDIENT

Active Ingredients: Taraxacum e pl. tota (Dandelion) 2X, Crataegus e fol. et fruct. (Hawthorn) 3X, Valeriana e rad. (Valerian) 3X, Cactus ex herba (Queen of the night) 4X, Camphora (Camphor) 4X, Strophanthus e sem. (Strophantus) 6X, Aurum metallicum (Metallic gold) 10X

Inactive Ingredients: Water, Salt

PURPOSE

Uses: Temporary relief of nausea and travel sickness.

KEEP OUT OF REACH OF CHILDREN.

WARNINGS

Warnings: Claims based on traditional homeopathic practice, not accepted medical evidence. Not FDA evaluated. Do not use if allergic to any ingredient. Consult a doctor before use for serious conditions or if conditions worsen or persist. If pregnant or nursing, consult a doctor before use.

QUESTIONS

Questions? Call 866.642.2858 Uriel, East Troy, WI 53120 www.urielpharmacy.com